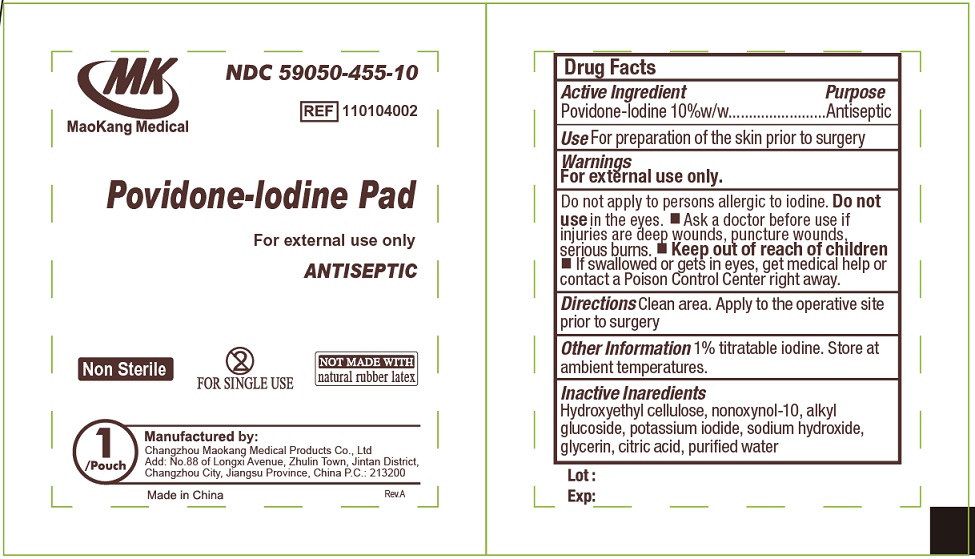 DRUG LABEL: Prep non sterile
NDC: 59050-455 | Form: PATCH
Manufacturer: Changzhou Maokang Medical Products Co., Ltd
Category: otc | Type: HUMAN OTC DRUG LABEL
Date: 20231115

ACTIVE INGREDIENTS: POVIDONE-IODINE 10 g/100 g
INACTIVE INGREDIENTS: HYDROXYETHYL CELLULOSE, UNSPECIFIED; NONOXYNOL-10; POTASSIUM IODIDE; SODIUM HYDROXIDE; GLYCERIN; CITRIC ACID MONOHYDRATE; WATER

Povidone-Iodine Prep Pad non-sterile

Active ingredient

Povidone-lodine 10%w/w

Purpose

Antiseptic

Use

For preparation of the skin prior to surgery

Warnings

For external use only.

Do not apply to persions allergic to iodine.

Do not use

in the eyes.

Ask a doctor before use if

injuries are deep wounds, puncture wounds, serious burns.

Keep out of reach of children

- If swallowed or gets in eyes, get medical help or contact a Poison Control Center right away.

Driections

Clean area. Apply to the operative site prior to surgery

Other information

1% titratable iodine. Store at ambient temperatures.

Inactive ingredients:

Hydroxyethyl cellulose, nonoxynol-10, alkyl glucoside, potassium iodide, sodium hydroxide, glycerin, citric acid, purifed water